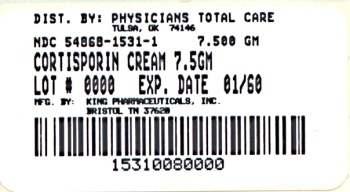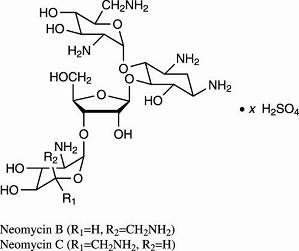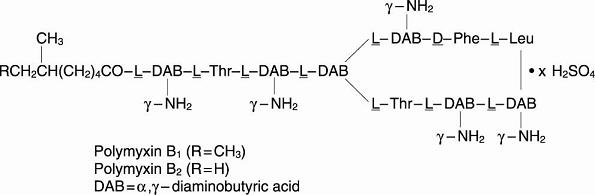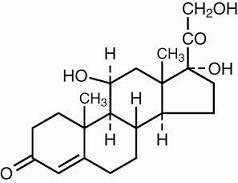 DRUG LABEL: Cortisporin
NDC: 54868-1531 | Form: CREAM
Manufacturer: Physicians Total Care, Inc.
Category: prescription | Type: HUMAN PRESCRIPTION DRUG LABEL
Date: 20101230

ACTIVE INGREDIENTS: NEOMYCIN SULFATE 3.5 mg/1 g; POLYMYXIN B SULFATE 10000 U/1 g; HYDROCORTISONE ACETATE 5 mg/1 g
INACTIVE INGREDIENTS: LIGHT MINERAL OIL; PETROLATUM; METHYLPARABEN; PROPYLENE GLYCOL; WATER

DESCRIPTION

CORTISPORIN Cream (neomycin and polymyxin B sulfates and hydrocortisone acetate cream, USP) is a topical antibacterial cream. Each gram contains: neomycin sulfate equivalent to 3.5 mg neomycin base, polymyxin B sulfate equivalent to 10,000 polymyxin B units, and hydrocortisone acetate 5 mg (0.5%). The inactive ingredients are liquid petrolatum, white petrolatum, propylene glycol, polyoxyethylene polyoxypropylene compound, emulsifying wax, purified water, and 0.25% methylparaben added as a preservative. Sodium hydroxide or sulfuric acid may be added to adjust pH.

Neomycin sulfate is the sulfate salt of neomycin B and C, which are produced by the growth of Streptomyces fradiae Waksman (Fam. Streptomycetaceae). It has a potency equivalent of not less than 600µg of neomycin standard per mg, calculated on an anhydrous basis. The structural formulae are:

Polymyxin B sulfate is the sulfate salt of polymyxin B1 and B2, which are produced by the growth of Bacillus polymyxa (Prazmowski) Migula (Fam. Bacillaceae). It has a potency of not less than 6,000 polymyxin B units per mg, calculated on an anhydrous basis. The structural formulae are:

Hydrocortisone acetate is the acetate ester of hydrocortisone, an anti-inflammatory hormone. Its chemical name is 21-(acetyloxy)- 11β,17-dihydroxypregn-4-ene-3,20-dione. Its structural formula is:

The base is a smooth vanishing cream with a pH of approximately 5.0.

CLINICAL PHARMACOLOGY

Corticoids suppress the inflammatory response to a variety of agents and they may delay healing. Since corticoids may inhibit the body’s defense mechanism against infection, a concomitant antimicrobial drug may be used when this inhibition is considered to be clinically significant in a particular case.

The anti-infective components in the combination are included to provide action against specific organisms susceptible to them. Polymyxin B sulfate and neomycin sulfate together are considered active against the following microorganisms: Staphylococcus aureus, Escherichia coli, Haemophilus influenzae, Klebsiella- Enterobacter species, Neisseria species, and Pseudomonas aeruginosa. The product does not provide adequate coverage against Serratia marcescens and streptococci, including Streptococcus pneumoniae.

The relative potency of corticosteroids depends on the molecular structure, concentration, and release from the vehicle.

The acid pH helps restore normal cutaneous acidity. Owing to its excellent spreading and penetrating properties, the cream facilitates treatment of hairy and intertriginous areas. It may also be of value in selective cases where the lesions are moist.

INDICATIONS AND USAGE

For the treatment of corticosteroid-responsive dermatoses with secondary infection. It has not been demonstrated that this steroid-antibiotic combination provides greater benefit than the steroid component alone after 7 days of treatment (see WARNINGS).

CONTRAINDICATIONS

Not for use in the eyes or in the external ear canal if the eardrum is perforated. This product is contraindicated in tuberculous, fungal, or viral lesions of the skin (herpes simplex, vaccinia, and varicella). This product is contraindicated in those individuals who have shown hypersensitivity to any of its components.

WARNINGS

Because of the concern of nephrotoxicity and ototoxicity associated with neomycin, this combination should not be used over a wide area or for extended periods of time.

PRECAUTIONS

General

As with any antibacterial preparation, prolonged use may result in overgrowth of nonsusceptible organisms, including fungi. Appropriate measures should be taken if this occurs. Use of steroids on infected areas should be supervised with care as anti-inflammatory steroids may encourage spread of infection. If this occurs, steroid therapy should be stopped and appropriate anti-bacterial drugs used. Generalized dermatological conditions may require systemic corticosteroid therapy.

Signs and symptoms of exogenous hyperadrenocorticism can occur with the use of topical corticosteroids, including adrenal suppression. Systemic absorption of topically applied steroids will be increased if extensive body surface areas are treated or if occlusive dressings are used. Under these circumstances, suitable precautions should be taken when long-term use is anticipated.

Specifically, sufficient percutaneous absorption of hydrocortisone can occur in pediatric patients during prolonged use to cause cessation of growth, as well as other systemic signs and symptoms of hyperadrenocorticism.

Information for Patients

If redness, irritation, swelling or pain persists or increases, discontinue use and notify physician. Do not use in the eyes.

Laboratory Tests

Systemic effects of excessive levels of hydrocortisone may include a reduction in the number of circulating eosinophils and a decrease in urinary excretion of 17-hydroxycorticosteroids.

Carcinogenesis, Mutagenesis, Impairment of Fertility

Longterm studies in animals (rats, rabbits, mice) showed no evidence of carcinogenicity attributable to oral administration of corticosteroids.

Pregnancy Teratogenic Effects

Pregnancy Category C. Corticosteroids have been shown to be teratogenic in rabbits when applied topically at concentrations of 0.5% on days 6 to 18 of gestation and in mice when applied topically at a concentration of 15% on days 10 to 13 of gestation. There are no adequate and well-controlled studies in pregnant women. Corticosteroids should be used during pregnancy only if the potential benefit justifies the potential risk to the fetus.

Nursing Mothers

Hydrocortisone acetate appears in human milk following oral administration of the drug. Since systemic absorption of hydrocortisone may occur when applied topically, caution should be exercised when CORTISPORIN Cream is used by a nursing woman.

Geriatric Use

Clinical studies of Cortisporin Cream did not include sufficient numbers of subjects aged 65 and over to determine whether they respond differently from younger subjects. Other reported clinical experience has not identified differences in responses between the elderly and younger patients. In general, dose selection for an elderly patient should be cautious, usually starting at the low end of the dosing range, reflecting the greater frequency of decreased hepatic, renal, or cardiac function, and of concomitant disease or other drug therapy.

Pediatric Use

Safety and effectiveness in pediatric patients have not been established (see PRECAUTIONS: General).

ADVERSE REACTIONS

Neomycin occasionally causes skin sensitization. Ototoxicity and nephrotoxicity have also been reported (see WARNINGS). Adverse reactions have occurred with topical use of antibiotic combinations including neomycin and polymyxin B. Exact incidence figures are not available since no denominator of treated patients is available. The reaction occurring most often is allergic sensitization. In one clinical study, using a 20% neomycin patch, neomycin-induced allergic skin reactions occurred in two of 2,175 (0.09%) individuals in the general population.^1 In another study, the incidence was found to be approximately 1%.^2

The following local adverse reactions have been reported with topical corticosteroids, especially under occlusive dressings: burning, itching, irritation, dryness, folliculitis, hypertrichosis, acneiform eruptions, hypopigmentation, perioral dermatitis, allergic contact dermatitis, maceration of the skin, secondary infection, skin atrophy, striae, and miliaria.

When steroid preparations are used for long periods of time in intertriginous areas or over extensive body areas, with or without occlusive non-permeable dressings, striae may occur; also there exists the possibility of systemic side effects when steroid preparations are used over large areas or for a long period of time.

DOSAGE AND ADMINISTRATION

A small quantity of the cream should be applied 2 to 4 times daily, as required. The cream should, if conditions permit, be gently rubbed into the affected areas.

HOW SUPPLIED

Tube of 7.5 g (NDC 54868-1531-1).

Store at 15° to 25°C (59° to 77°F).

References

1. Leyden JJ, Kligman AM. Contact dermatitis to neomycin sulfate. JAMA. 1979;242:1276-1278.
2. Prystowsky SD, Allen AM, Smith RW, et al. Allergic contact hypersensitivity to nickel, neomycin, ethylenediamine, and benzocaine. Arch Dermatol. 1979;115:959-962.

Prescribing Information as of November 2003.

Distributed by: Monarch Pharmaceuticals, Inc., Bristol, TN 37620

(A wholly owned subsidiary of King Pharmaceuticals, Inc.)

Manufactured by: King Pharmaceuticals, Inc., Bristol, TN 37620

Relabeling of "Additional Barcode" label by:
Physicians Total Care, Inc.
Tulsa, OK 74146

PRINCIPAL DISPLAY PANEL

CORTISPORIN Cream (neomycin and polymyxin B sulfates and hydrocortisone acetate cream, USP)